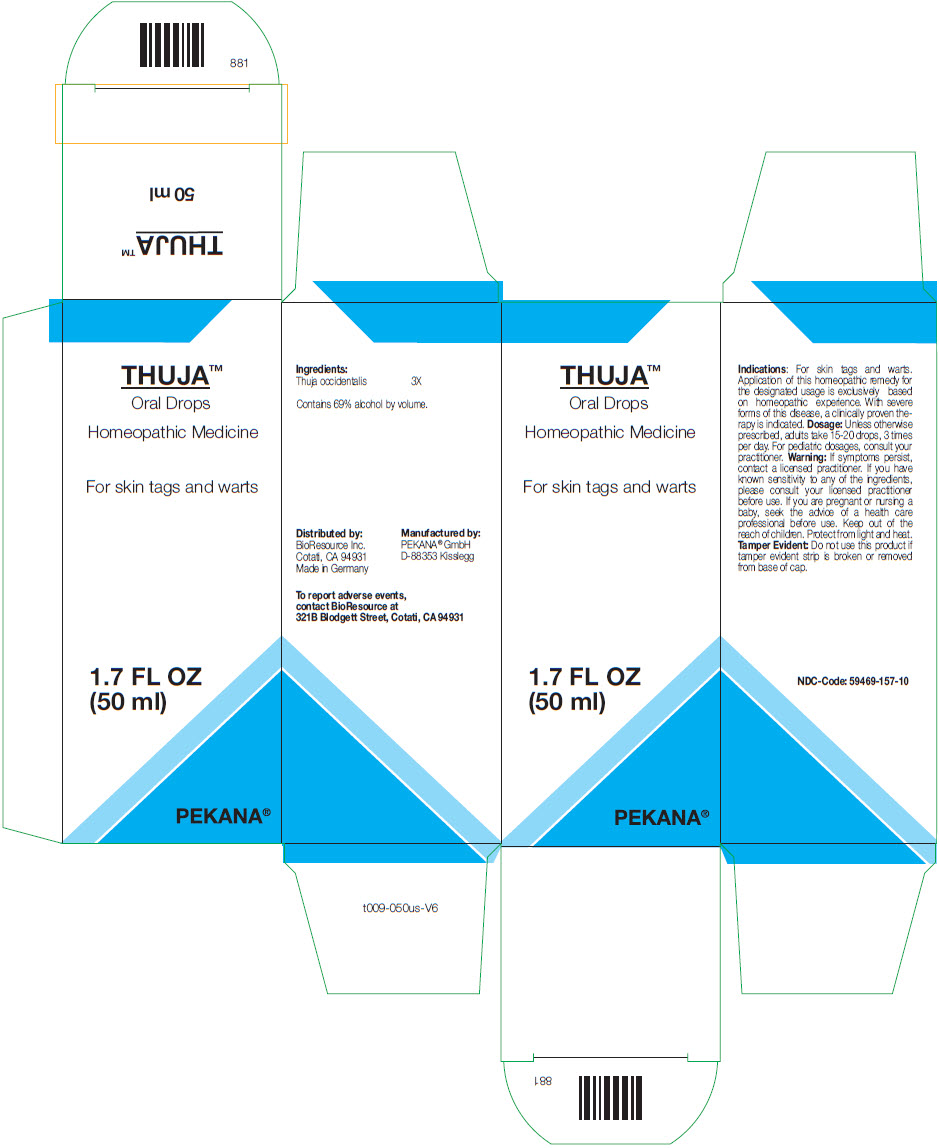 DRUG LABEL: Thuja
NDC: 59469-157 | Form: LIQUID
Manufacturer: PEKANA Naturheilmittel GmbH
Category: homeopathic | Type: HUMAN OTC DRUG LABEL
Date: 20221223

ACTIVE INGREDIENTS: Thuja occidentalis leafy twig 3 [hp_X]/50 mL
INACTIVE INGREDIENTS: Alcohol

Thuja™

Indications

PURPOSE

For skin tags and warts. Application of this homeopathic remedy for the designated usage is exclusively based on homeopathic experience. With severe forms of this disease, a clinically proven therapy is indicated.

Dosage

Unless otherwise prescribed, adults take 15-20 drops, 3 times per day. For pediatric dosages, consult your practitioner.

Warning

ASK DOCTOR

If symptoms persist, contact a licensed practitioner. If you have known sensitivity to any of the ingredients, please consult your licensed practitioner before use. If you are pregnant or nursing a baby, seek the advice of a health care professional before use.

Keep out of the reach of children.

STORAGE AND HANDLING

Protect from light and heat.

Tamper Evident

Do not use this product if tamper evident strip is broken or removed from base of cap.

Ingredients

Thuja occidentalis | 3X

INACTIVE INGREDIENT

Contains 69% alcohol by volume.

QUESTIONS

To report adverse events, contact BioResource at 321B Blodgett Street, Cotati, CA 94931

Manufactured by:
PEKANA® GmbH
D-88353 Kisslegg

Distributed by: BioResource Inc.
Cotati, CA 94931

PRINCIPAL DISPLAY PANEL - 50 ml Bottle Box

THUJA™
Oral Drops

Homeopathic Medicine

For skin tags and warts

1.7 FL OZ
(50 ml)

PEKANA®